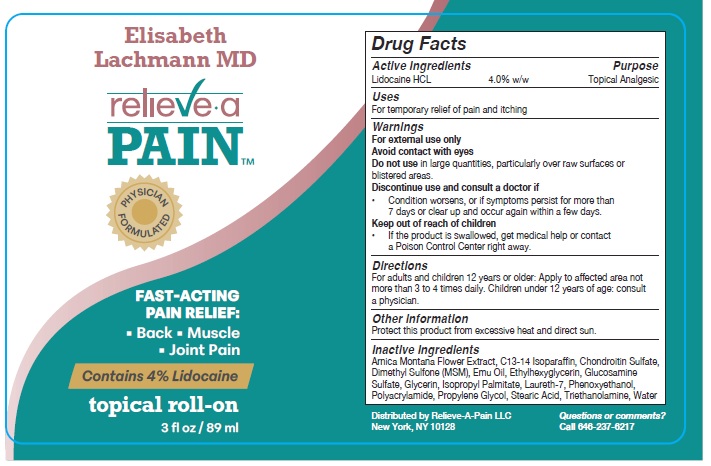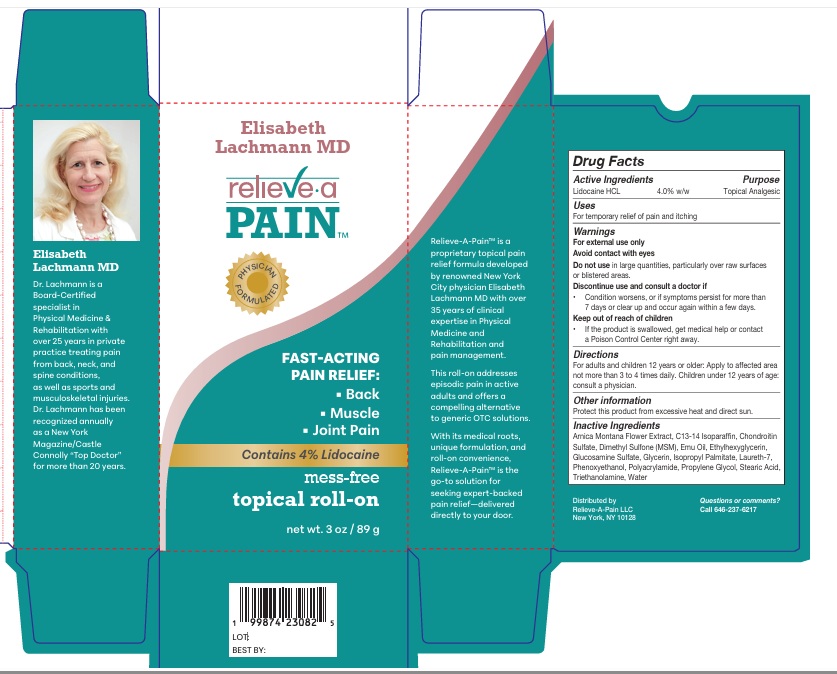 DRUG LABEL: Relieve A Pain
NDC: 87198-001 | Form: LOTION
Manufacturer: Relieve A Pain LLC
Category: otc | Type: HUMAN OTC DRUG LABEL
Date: 20260108

ACTIVE INGREDIENTS: LIDOCAINE 4 g/100 g
INACTIVE INGREDIENTS: ARNICA MONTANA FLOWER; C13-14 ISOPARAFFIN; SODIUM CHONDROITIN SULFATE (PORCINE; 5500 MW); DIMETHYL SULFONE; EMU OIL; ETHYLHEXYLGLYCERIN; GLUCOSAMINE SULFATE; GLYCERIN; ISOPROPYL PALMITATE; LAURETH-7; PHENOXYETHANOL; POLYACRYLAMIDE (1500 MW); PROPYLENE GLYCOL; STEARIC ACID; TROLAMINE; WATER

Active Ingredients

Lidocaine HCL 4.0% w/w

Purpose

Topical Analgesic

Uses

For temporary relief of pain and itching.

Warnings

For external use only

Avoid contact with eyes

Do not use in large quantities, particularly over raw surfaces or blistered areas.

Discontinue use and consult a doctor if

• Condition worsens, or if symptoms persist for more than 7 days or clear up and occur again within a few days.

Keep out of reach of children

• If the product is swallowed, get medical help or contact a Poison Control Center right away.

Directions

For adults and children 12 years or older: Apply to affected area not more than 3 to 4 times daily.

Children under 12 years of age: consult a physician.

Other information

Protect this product from excessive heat and direct sun.

Inactive Ingredients

Arnica Montana Flower Extract, C13-14 Isoparaffin, Chondroitin Sulfate, Dimethyl Sulfone (MSM), Emu Oil, Ethylhexylglycerin, Glucosamine Sulfate, Glycerin, Isopropyl Palmitate, Laureth-7, Phenoxyethanol, Polyacrylamide, Propylene Glycol, Stearic Acid, Triethanolamine, Water